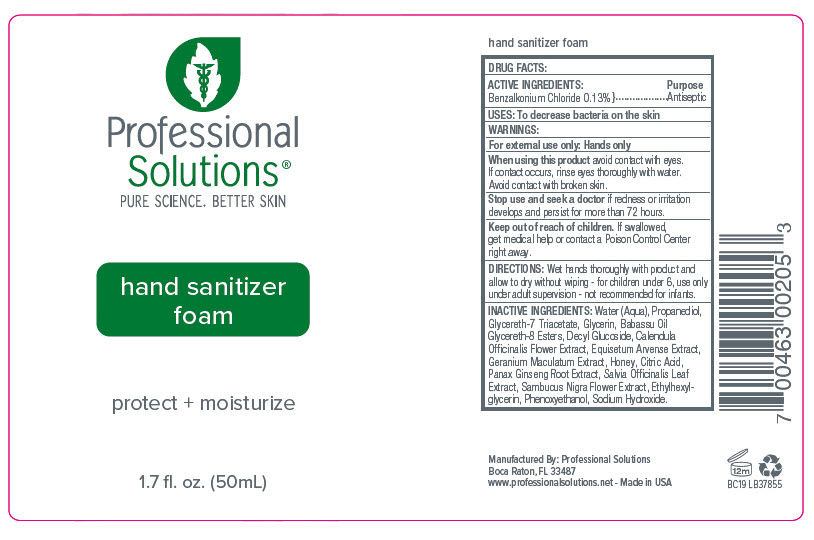 DRUG LABEL: Professional Solutions - Hand Sanitizer Foam
NDC: 66163-1900 | Form: LIQUID
Manufacturer: Cosmetic Solutions LLC
Category: otc | Type: HUMAN OTC DRUG LABEL
Date: 20200714

ACTIVE INGREDIENTS: BENZALKONIUM CHLORIDE 1.3 mg/10 mL
INACTIVE INGREDIENTS: Water; Propanediol; Glycereth-7 Triacetate; Glycerin; Babassu Oil Glycereth-8 Esters; Decyl Glucoside; Calendula Officinalis Flower; Equisetum Arvense Branch; Geranium Maculatum Root; Honey; Citric Acid Monohydrate; Asian Ginseng; Sambucus Nigra Flower; Ethylhexylglycerin; Phenoxyethanol; Sodium Hydroxide

Professional Solutions® - Hand Sanitizer Foam

DRUG FACTS:

ACTIVE INGREDIENTS

Benzalkonium Chloride 0.13%

Purpose

Antiseptic

USES

To decrease bacteria on the skin

WARNINGS

For external use only: Hands only

When using this product avoid contact with eyes. If contact occurs, rinse eyes thoroughly with water. Avoid contact with broken skin.

Stop use and seek a doctor if redness or irritation develops and persist for more than 72 hours.

Keep out of reach of children. If swallowed, get medical help or contact a Poison Control Center right away.

DIRECTIONS

Wet hands thoroughly with product and allow to dry without wiping - for children under 6, use only under adult supervision - not recommended for infants.

INACTIVE INGREDIENTS

Water (Aqua), Propanediol, Glycereth-7 Triacetate, Glycerin, Babassu Oil Glycereth-8 Esters, Decyl Glucoside, Calendula Officinalis Flower Extract, Equisetum Arvense Extract, Geranium Maculatum Extract, Honey, Citric Acid, Panax Ginseng Root Extract, Salvia Officinalis Leaf Extract, Sambucus Nigra Flower Extract, Ethylhexylglycerin, Phenoxyethanol, Sodium Hydroxide.

Manufactured By: Professional Solutions
Boca Raton, FL 33487

PRINCIPAL DISPLAY PANEL - 50 mL Bottle Label

Professional
Solutions®
PURE SCIENCE. BETTER SKIN

hand sanitizer
foam

protect + moisturize

1.7 fl. oz. (50mL)